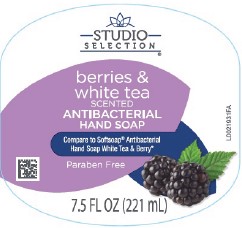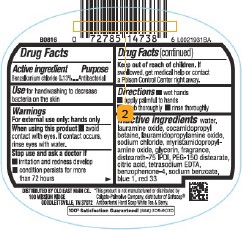 DRUG LABEL: Antibacterial
NDC: 75712-897 | Form: SOAP
Manufacturer: Old East Main Co.
Category: otc | Type: HUMAN OTC DRUG LABEL
Date: 20260302

ACTIVE INGREDIENTS: BENZALKONIUM CHLORIDE 1.3 mg/1 mL
INACTIVE INGREDIENTS: WATER; LAURAMINE OXIDE; COCAMIDOPROPYL BETAINE; LAURAMIDOPROPYLAMINE OXIDE; SODIUM CHLORIDE; MYRISTAMIDOPROPYLAMINE OXIDE; GLYCERIN; DISTEARETH-75 ISOPHORONE DIISOCYANATE; PEG-150 DISTEARATE; CITRIC ACID MONOHYDRATE; EDETATE SODIUM; SULISOBENZONE; SODIUM BENZOATE; FD&C BLUE NO. 1; D&C RED NO. 33

Studio Selection 897.003/897AC
Antibacterial Hand Soap Berries & White Tea

Active Ingredient

Benzalkonium chloride 0.13%

Purpose

Antibacterial

Use

for handwashing to decrease bacteria on the skin

Warnings

For external use only: hands only

When using this product

- avoid contact with eyes. If contact occurs, rinse eyes with water.

stop use and ask a doctor if

- if irritation and redness develop
- comdition persists for more than 72 hours

Keep out of reach of children.

If swallowed, get medical help or contact a Poison Control Center right away.

Directions

- wet hands
- apply palmful to hands
- scrub thoroughly
- rinse thoroughly

Inactive ingredients

water, lauramine oxide, cocamidopropyl betaine, lauramidopropylamine oxide, sodium chloride, myristamidopropylamine oxide, glycerin, fragrance, disteareth-75 IPDI, PEG-150 distearate, citric acid, tetrasodium EDTA, benzophenone-4, sodium benzoate, blue 1, red 33

Disclaimer

*This product is not manufactured or distributed by the Colgate-Palmolive Company, distributor of SoftsoapAntibacterial Hand Soap White Tea & Berry.

Adverse reaction

DISTRIBUTED BY OLD EAST MAIN CO.

100 MISSION RIDGE

GOODLETTSVILLE, TN 37072

100% Satsifaction Guaranteed! (888) 309-9030

Principal Panel Display

STUDIO SELECTION®

berries & white tea

SCENTED

ANTIBACTERIAL HAND SOAP

Compare to Softsoap® Antibacterial Hand Soap White Tea & Berry*

Paraben Free

7.5 FL OZ (221 mL)